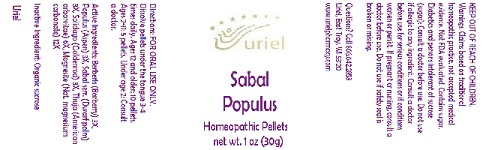 DRUG LABEL: Sabal Populus
NDC: 48951-8159 | Form: PELLET
Manufacturer: Uriel Pharmacy Inc.
Category: homeopathic | Type: HUMAN OTC DRUG LABEL
Date: 20180606

ACTIVE INGREDIENTS: BERBERIS VULGARIS ROOT BARK 3 [hp_X]/1 1; POPULUS TREMULA WHOLE 3 [hp_X]/1 1; SAW PALMETTO 3 [hp_X]/1 1; SOLIDAGO VIRGAUREA FLOWERING TOP 3 [hp_X]/1 1; THUJA OCCIDENTALIS WHOLE 6 [hp_X]/1 1; MAGNESITE 12 [hp_X]/1 1
INACTIVE INGREDIENTS: SUCROSE

Sabal Populus

INDICATIONS AND USAGE

Directions: FOR ORAL USE ONLY.

DOSAGE AND ADMINISTRATION

Dissolve pellets under the tongue 3-4 times daily. Ages 12 and older: 10 pellets. Ages 2-11: 5 pellets. Under age 2: Consult a doctor.

ACTIVE INGREDIENT

Active Ingredients: Berberis (Barberry) 3X, Populus (Aspen) 3X, Sabal serr. (Dwarf palm) 3X, Solidago (Goldenrod) 3X, Thuja (American arborvitae) 6X, Magnesite (Nat. magnesium carbonate) 12X

Inactive Ingredient: Organic sucrose

PURPOSE

Use: Temporary relief of headache.

KEEP OUT OF REACH OF CHILDREN.

WARNINGS

Warnings: Claims based on traditional homeopathic practice, not accepted medical evidence. Not FDA evaluated. Contains sugar. Diabetics and persons intolerant of sucrose (sugar): Consult a doctor before use. Do not use if allergic to any ingredient. Consult a doctor before use for serious conditions or if conditions worsen or persist. If pregnant or nursing, consult a doctor before use. Do not use if safety seal is broken or missing.

QUESTIONS

Questions? Call 866.642.2858 Uriel, East Troy, WI 53120 www.urielpharmacy.com